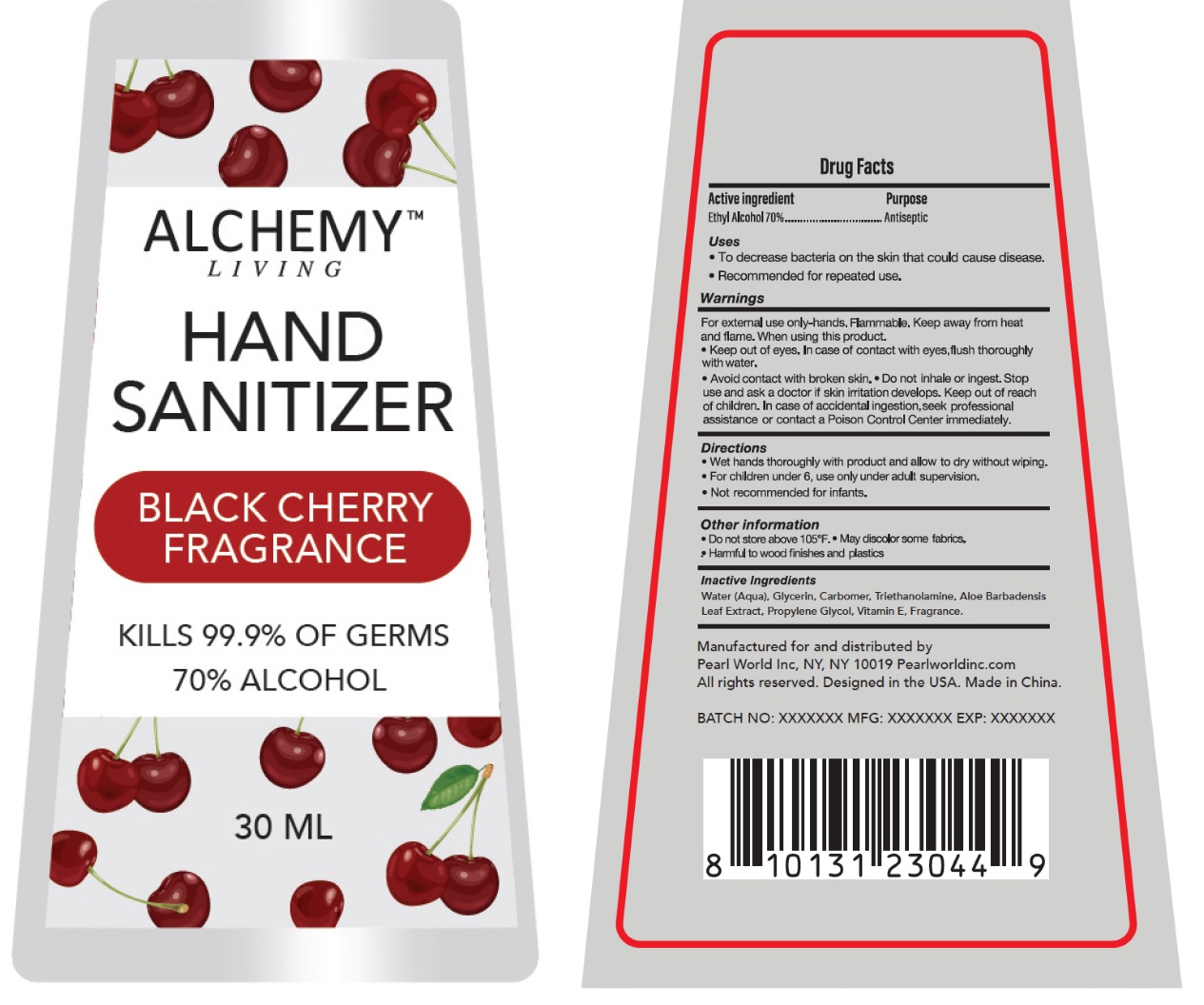 DRUG LABEL: ALCHEMY LIVING HAND SANITIZER BLACK CHERRY FRAGRANCE
NDC: 69933-440 | Form: LIQUID
Manufacturer: Pearl World Inc.
Category: otc | Type: HUMAN OTC DRUG LABEL
Date: 20230415

ACTIVE INGREDIENTS: ALCOHOL 70 mL/100 mL
INACTIVE INGREDIENTS: WATER; GLYCERIN; CARBOMER HOMOPOLYMER, UNSPECIFIED TYPE; TROLAMINE; ALOE VERA LEAF; PROPYLENE GLYCOL; .ALPHA.-TOCOPHEROL

ALCHEMY™ LIVING HAND SANITIZER BLACK CHERRY FRAGRANCE

Active ingredient

Ethyl Alcohol 70%

Purpose

Antiseptic

Uses

• To decrease bacteria on the skin that could cause disease.
• Recommended for repeated use.

Warnings

For external use only-hands. Flammable. Keep away from heat and flame. When using this product.
• Keep out of eyes. In case of contact with eyes, flush thoroughly with water.
• Avoid contact with broken skin. • Do not inhale or ingest. Stop use and ask a doctor if skin irritation develops.

Keep out of reach of children. In case of accidental ingestion, seek professional assistance or contact a Poison Control Center immediately.

Directions

• Wet hands thoroughly with product and allow to dry without wiping.
• For children under 6, use only under adult supervision.
• Not recommended for infants.

Other information

• Do not store above 105°F. • May discolor some fabrics.
• Harmful to wood finishes and plastics

Inactive Ingredients

Water (Aqua), Glycerin, Carbomer, Triethanolamine, Aloe Barbadensis Leaf Extract, Propylene Glycol, Vitamin E, Fragrance.

KILLS 99.9% OF GERMS

Manufactured for and distributed by
Pearl World Inc, NY, NY 10019 Pearlworldinc.com
All rights reserved. Designed in the USA. Made in China.